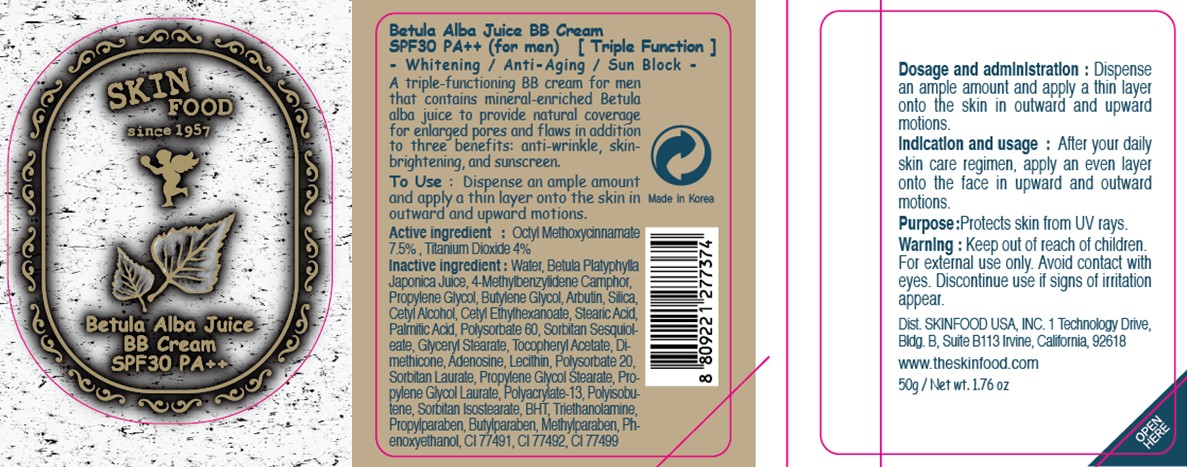 DRUG LABEL: BETULA ALBA JUICE BB
NDC: 76214-036 | Form: CREAM
Manufacturer: SKINFOOD CO., LTD.
Category: otc | Type: HUMAN OTC DRUG LABEL
Date: 20111009

ACTIVE INGREDIENTS: OCTINOXATE 3.75 g/50 g; TITANIUM DIOXIDE 2 g/50 g
INACTIVE INGREDIENTS: WATER; BETULA PLATYPHYLLA VAR. JAPONICA RESIN; PROPYLENE GLYCOL; BUTYLENE GLYCOL; ARBUTIN; SILICON DIOXIDE; CETYL ALCOHOL; CETYL ETHYLHEXANOATE; STEARIC ACID; PALMITIC ACID; POLYSORBATE 60; SORBITAN SESQUIOLEATE; GLYCERYL MONOSTEARATE; DIMETHICONE; ADENOSINE; LECITHIN, SOYBEAN; POLYSORBATE 20; SORBITAN MONOLAURATE; PROPYLENE GLYCOL MONOSTEARATE; BUTYLATED HYDROXYTOLUENE; TROLAMINE; PROPYLPARABEN; BUTYLPARABEN; METHYLPARABEN; PHENOXYETHANOL

Drug Facts

Active ingredients: OCTINOXATE 7.5%, Titanium Dioxide 4%

Inactive ingredients:
Water, Betula Platyphylla Japonica Juice, 4-Methylbenzylidene Camphor, Propylene Glycol, Butylene Glycol, Arbutin, Silica, Cetyl Alcohol, Cetyl Ethylhexanoate, Stearic Acid, Palmitic Acid, Polysorbate 60, Sorbitan Sesquioleate, Glyceryl Stearate, Tocopheryl Acetate, Dimethicone, Adenosine, Lecithin, Polysorbate 20, Sorbitan Laurate, Propylene Glycol Stearate, Propylene Glycol Laurate, Polyacrylate-13, Polyisobutene, Sorbitan Isostearate, BHT, Triethanolamine, Propylparaben, Butylparaben, Methylparaben, Phenoxyethanol, CI 77491, CI 77492, CI 77499

Purpose: Protects skin from UV rays.

Warnings:
For external use only.
Avoid contact with eyes.
Discontinue use if signs of irritation appear.

Keep out of reach of children:
Keep out of reach of children.

Indication and usage:
After your daily skin care regimen, apply an even layer onto the face in upward and outward motions.

Dosage and administration:
Dispense an ample amount and apply a thin layer onto the skin in outward and upward motions.